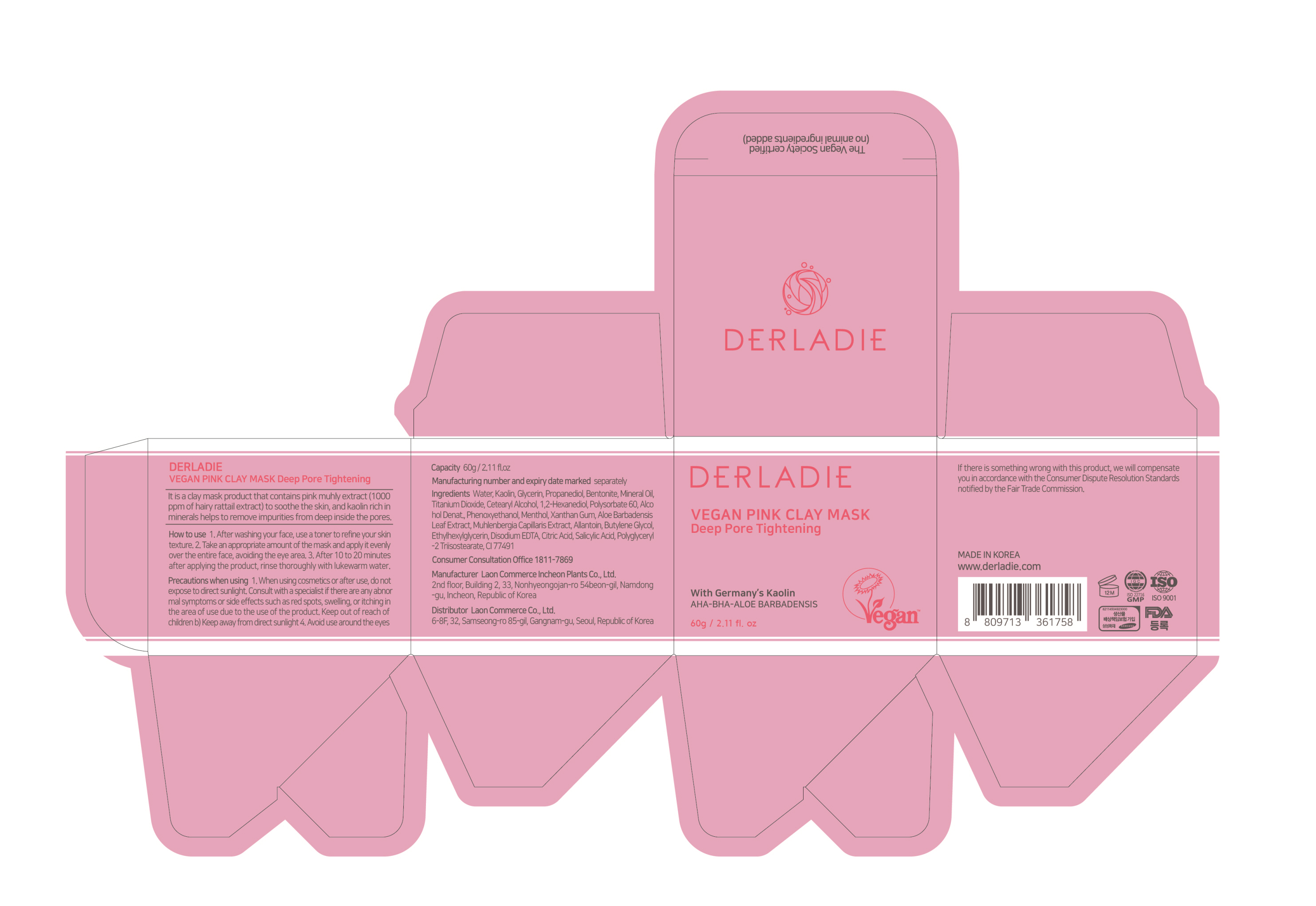 DRUG LABEL: Derladie Vegan Pink Clay Mask Deep Pore Tightening
NDC: 82083-0027 | Form: CREAM
Manufacturer: LAON COMMERCE co ltd
Category: otc | Type: HUMAN OTC DRUG LABEL
Date: 20231206

ACTIVE INGREDIENTS: KAOLIN 25 g/100 g
INACTIVE INGREDIENTS: WATER; ALOE VERA LEAF

ACTIVE INGREDIENT

Kaolin

INACTIVE INGREDIENT

Water
Glycerin
Propanediol
Bentonite
Mineral Oil
Titanium Dioxide
Cetearyl Alcohol
1,2-Hexanediol
Polysorbate 60
Alcohol Denat.
Phenoxyethanol
Menthol
Xanthan Gum
Aloe Barbadensis Leaf Extract
Muhlenbergia Capillaris Extract
Allantoin
Butylene Glycol
Ethylhexylglycerin
Disodium EDTA
Citric Acid
Salicylic Acid
Polyglyceryl-2 Triisostearate
CI 77491

PURPOSE

skin protect

KEEP OUT OF REACH OF THE CHILDREN

INDICATIONS AND USAGE

After washing your face, use a toner to refine your skin texture. 2. Take an appropriate amount of the mask and apply it evenly over the entire face, avoiding the eye area. 3. After 10 to 20 minutes after applying the product, rinse thoroughly with lukewarm water

WARNINGS

When using cosmetics or after use, do not expose to direct sunlight. Consult with a specialist if there are any abnormal symptoms or side effects such as red spots, swelling, or itching in the area of use due to the use of the product. Keep out of reach of children b) Keep away from direct sunlight . Avoid use around the eyes

DOSAGE AND ADMINISTRATION

topical use only